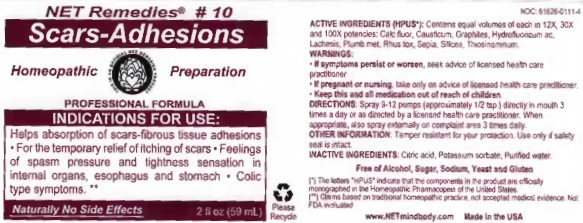 DRUG LABEL: Scars-Adhesions
NDC: 61626-0111 | Form: LIQUID
Manufacturer: NET Remedies
Category: homeopathic | Type: HUMAN PRESCRIPTION DRUG LABEL
Date: 20210121

ACTIVE INGREDIENTS: CALCIUM FLUORIDE 12 [hp_X]/59.1 mL; CAUSTICUM 12 [hp_X]/59.1 mL; GRAPHITE 12 [hp_X]/59.1 mL; HYDROFLUORIC ACID 12 [hp_X]/59.1 mL; LACHESIS MUTA VENOM 12 [hp_X]/59.1 mL; LEAD 12 [hp_X]/59.1 mL; TOXICODENDRON PUBESCENS LEAF 12 [hp_X]/59.1 mL; SEPIA OFFICINALIS JUICE 12 [hp_X]/59.1 mL; SILICON DIOXIDE 12 [hp_X]/59.1 mL; ALLYLTHIOUREA 12 [hp_X]/59.1 mL
INACTIVE INGREDIENTS: CITRIC ACID MONOHYDRATE; POTASSIUM SORBATE; WATER

Scars-Adhesions

ACTIVE INGREDIENT

ACTIVE INGREDIENTS (HPUS*): Contains equal volumes of each in 12X, 30X, and 100X potencies: Calc fluor, Causticum, Graphites, Hydrofluoricum ac, Lachesis, Plumb met, Rhus tox, Sepia, Silicea, Thiosinaminum.

(*) The letters "HPUS" indicate that the components in the product are offically monographed in the Homeopathic Pharmacopeia of the United States.

(**) Claims based on traditional homeopathic practice, not accepted medical evidence. Not FDA evaluated.

INDICATIONS AND USAGE

INDICATIONS FOR USE: Helps absorption of scars-fibrous tissue adhesions • For the temporary relief of itching of scars • Feelins of spasm pressure and tightness sensation in internal organs, esophagus and stomach • Colic type symptoms.**

WARNINGS

• If symptoms persist or worsen, seek advice of licensed health care practicioner.

• If pregnant or nursing, take on only advice of licensed health care practitioner.

• Keep this and all medication out of reach of children.

KEEP OUT OF REACH OF CHILDREN

• Keep this and all medication out of reach of children.

DOSAGE AND ADMINISTRATION

DIRECTIONS: Spray 9-12 pumps (approximately 1/2 tsp.) directly in mouth 3 times a day or as directed by a licensed health care practicioner. When appropriate, also spray externally on complaint area 3 times daily.

OTHER INFORMATION: Tamper resistant for your protection. Use only if safetly seal is intact.

INACTIVE INGREDIENTS: Citric acid, Potassium sorbate, Purified water.

Free of Alcohol, Sugar, Sodium, Yeast and Gluten

QUESTIONS

www.NETmindbody.com

Made in the USA

PACKAGE LABEL

NET Remedies

Scars-Adhesions

Homeopathic Preparation

PROFESSIONAL FORMULA

Naturally No Side Effects

2 fl oz (59 mL)

PURPOSE

INDICATIONS FOR USE: Helps absorption of scars-fibrous tissue adhesions • For the temporary relief of itching of scars • Feelins of spasm pressure and tightness sensation in internal organs, esophagus and stomach • Colic type symptoms.**